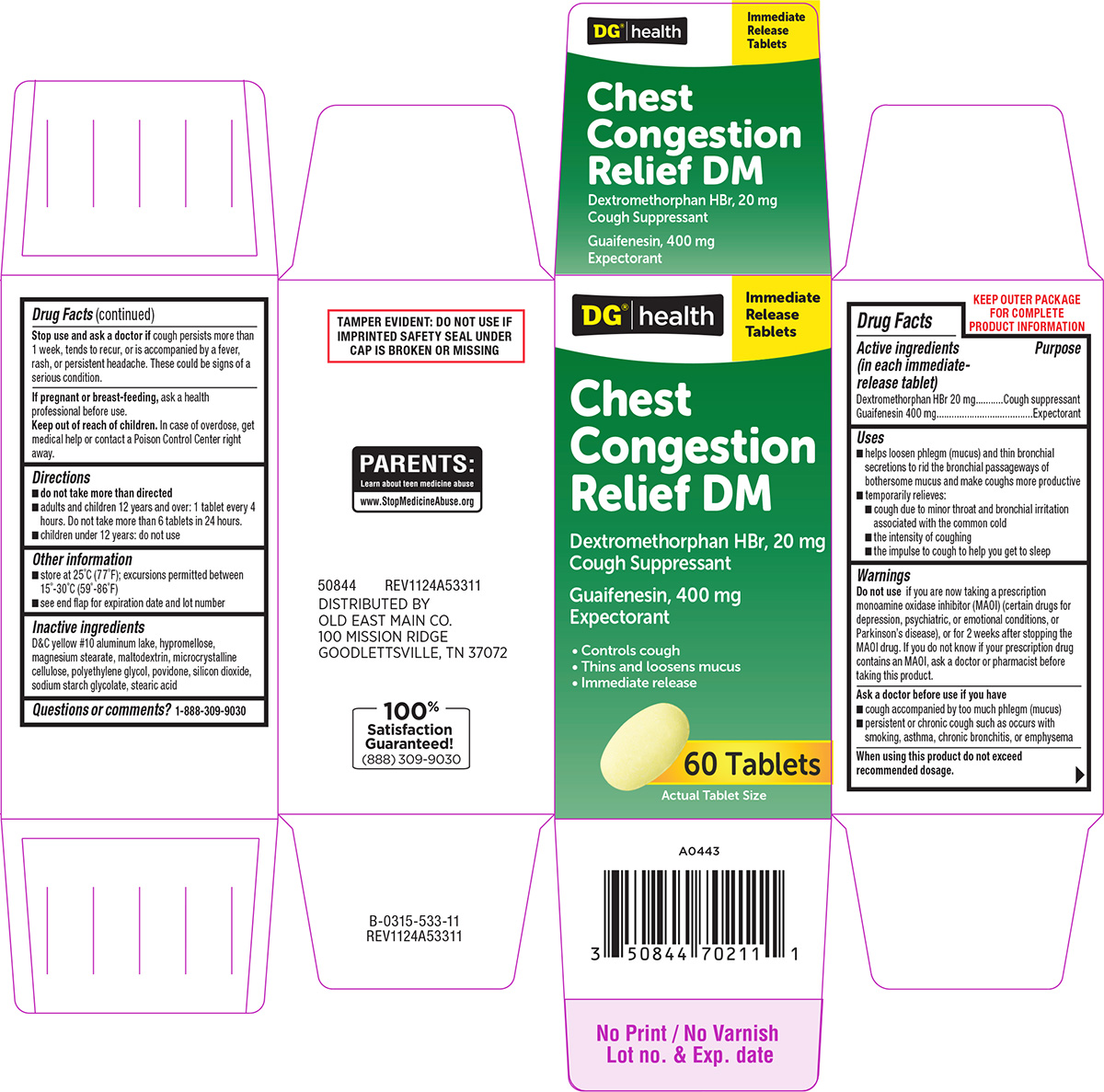 DRUG LABEL: Chest Congestion Relief DM
NDC: 55910-533 | Form: TABLET, FILM COATED
Manufacturer: DOLGENCORP, LLC
Category: otc | Type: HUMAN OTC DRUG LABEL
Date: 20250818

ACTIVE INGREDIENTS: DEXTROMETHORPHAN HYDROBROMIDE 20 mg/1 1; GUAIFENESIN 400 mg/1 1
INACTIVE INGREDIENTS: D&C YELLOW NO. 10 ALUMINUM LAKE; HYPROMELLOSE, UNSPECIFIED; MAGNESIUM STEARATE; MALTODEXTRIN; MICROCRYSTALLINE CELLULOSE; POLYETHYLENE GLYCOL, UNSPECIFIED; POVIDONE, UNSPECIFIED; SILICON DIOXIDE; SODIUM STARCH GLYCOLATE TYPE A POTATO; STEARIC ACID

Dollar General 44-533

Active ingredients (in each immediate-release tablet)

Dextromethorphan HBr 20 mg
Guaifenesin 400 mg

Purpose

Cough suppressant
Expectorant

Uses

- helps loosen phlegm (mucus) and thin bronchial secretions to rid the bronchial passageways of bothersome mucus and make coughs more productive
- temporarily relieves:
  - cough due to minor throat and bronchial irritation associated with the common cold
  - the intensity of coughing
  - the impulse to cough to help you get to sleep

Warnings

Do not use

if you are now taking a prescription monoamine oxidase inhibitor (MAOI) (certain drugs for depression, psychiatric, or emotional conditions, or Parkinson’s disease), or for 2 weeks after stopping the MAOI drug. If you do not know if your prescription drug contains an MAOI, ask a doctor or pharmacist before taking this product.

Ask a doctor before use if you have

- cough accompanied by too much phlegm (mucus)
- persistent or chronic cough such as occurs with smoking, asthma, chronic bronchitis, or emphysema

When using this product

do not exceed recommended dosage.

Stop use and ask a doctor if

cough persists more than 1 week, tends to recur, or is accompanied by a fever, rash, or persistent headache. These could be signs of a serious condition.

If pregnant or breast-feeding,

ask a health professional before use.

Keep out of reach of children.

In case of overdose, get medical help or contact a Poison Control Center right away.

Directions

- do not take more than directed
- adults and children 12 years and over: 1 tablet every 4 hours. Do not take more than 6 tablets in 24 hours.
- children under 12 years: do not use

Other information

- store at 25ºC (77ºF); excursions permitted between 15º-30ºC (59º-86ºF)
- see end flap for expiration date and lot number

Inactive ingredients

D&C yellow #10 aluminum lake, hypromellose, magnesium stearate, maltodextrin, microcrystalline cellulose, polyethylene glycol, povidone, silicon dioxide, sodium starch glycolate, stearic acid

Questions or comments?

1-888-309-9030

Principal display panel

DG® | health

Immediate
Release
Tablets

Chest
Congestion
Relief DM

Dextromethorphan HBr, 20 mg
Cough Suppressant

Guaifenesin, 400 mg
Expectorant

• Controls cough
• Thins and loosens mucus
• Immediate release

60 Tablets

Actual Tablet Size

TAMPER EVIDENT: DO NOT USE IF
IMPRINTED SAFETY SEAL UNDER
CAP IS BROKEN OR MISSING

PARENTS:
Learn about teen medicine abuse
www.StopMedicineAbuse.org

50844 REV1124A53311

DISTRIBUTED BY
OLD EAST MAIN CO.
100 MISSION RIDGE
GOODLETTSVILLE, TN 37072

100%
Satisfaction
Guaranteed!
(888) 309-9030

Dollar General 44-533